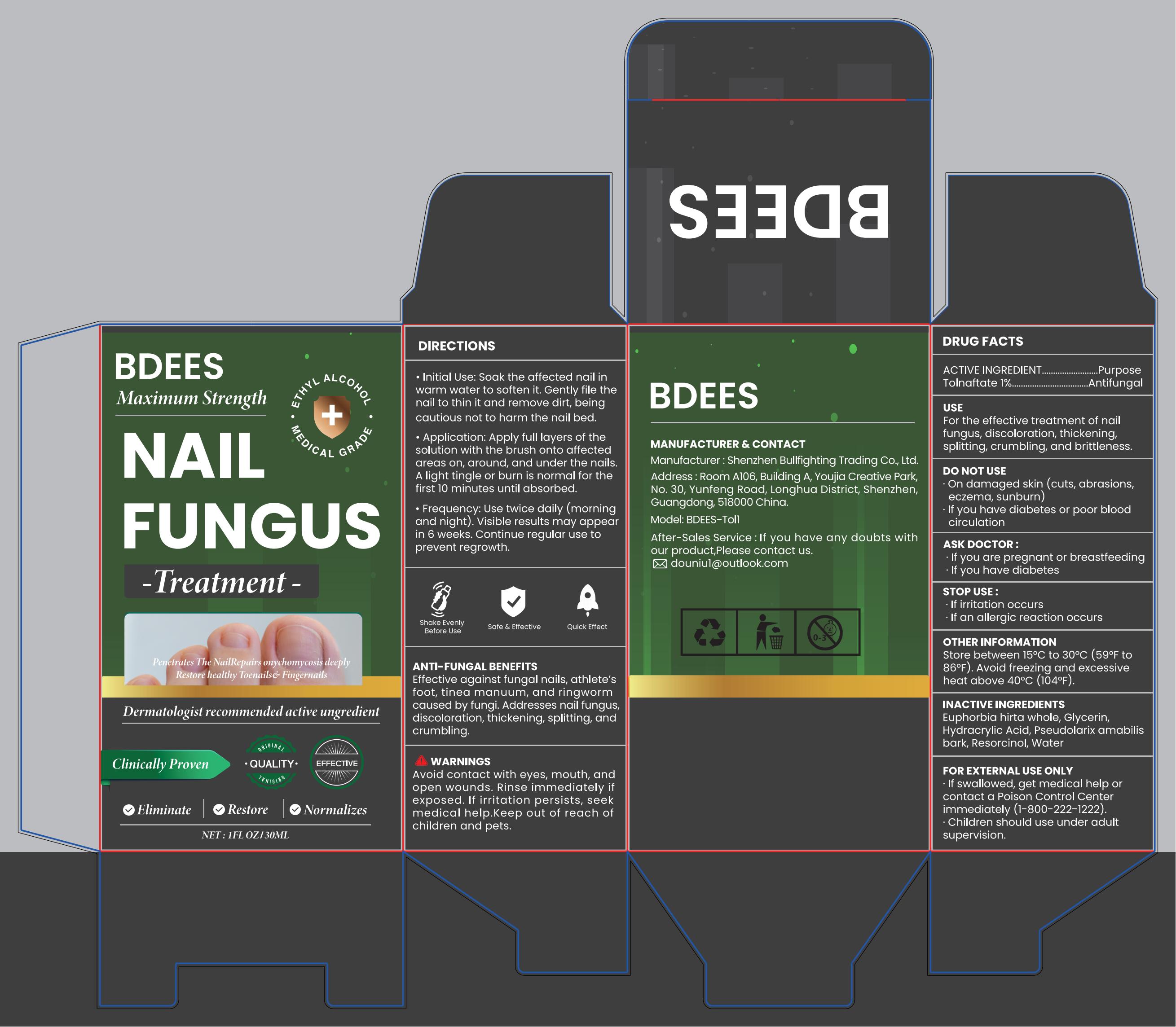 DRUG LABEL: NAIL FUNGUS TREATMENT
NDC: 85834-001 | Form: LIQUID
Manufacturer: Shenzhen Bullfighting Trading Co., Ltd.
Category: otc | Type: HUMAN OTC DRUG LABEL
Date: 20250629

ACTIVE INGREDIENTS: TOLNAFTATE 1 g/100 mL
INACTIVE INGREDIENTS: GLYCERIN; EUPHORBIA HIRTA WHOLE; HYDRACRYLIC ACID; PSEUDOLARIX AMABILIS BARK; RESORCINOL; WATER

85834-001

Active Ingredient

Tolnaftate 1%

Purpose

Antifungal

Use

For the effective treatment of nailfungus, discoloration, thickening,splitting, crumbling, and brittleness.

Warnings

Avoid contact with eyes, mouth, andopen wounds. Rinse immediately ifexposed.If irritation persists, seekmedical help.keep out of reach ofchildren and pets.

Do not use

On damaged skin (cuts, abrasions,eczema, sunburn).

lfyou have diabetes or poor bloodcirculation.

When Using

Skin discoloration may occur during or after use.

Stop Use

If irritation occurs. If an allergic reaction occurs.

Ask Doctor

if you are pregnant or breastfeeding.
if you have diabetes.

Keep out of reach of children and pets.

If swallowed, get medical help or contact a Poison Control Center immediately (1-800-222-1222).
Children should use under adult supervision.

Directions

Soak the affected nail inwarm water to soften it. Gently file thenail to thin it and remove dirt, beingcautious not to harm the nail bed.
Application: Apply full layers of thesolution with the brush onto affectedareas on, around, and under the nails.A light tingle or burn is normal for thefirst 10 minutes until absorbed.
Frequency: Use twice daily (morningand night). Visible results may appearin 6 weeks. Continue regular use toprevent regrowth.

Other information

Store between 15°C to 30'C(59'F to86°F). Avoid freezing and excessiveheat above 40°C (104°F).

Inactive ingredients

Euphorbia hirta whole, Glycerin, Hydracrylic Acid, Pseudolarix amabilis bark, Resorcinol, Water

Questions

Email: douniu1@outlook.com